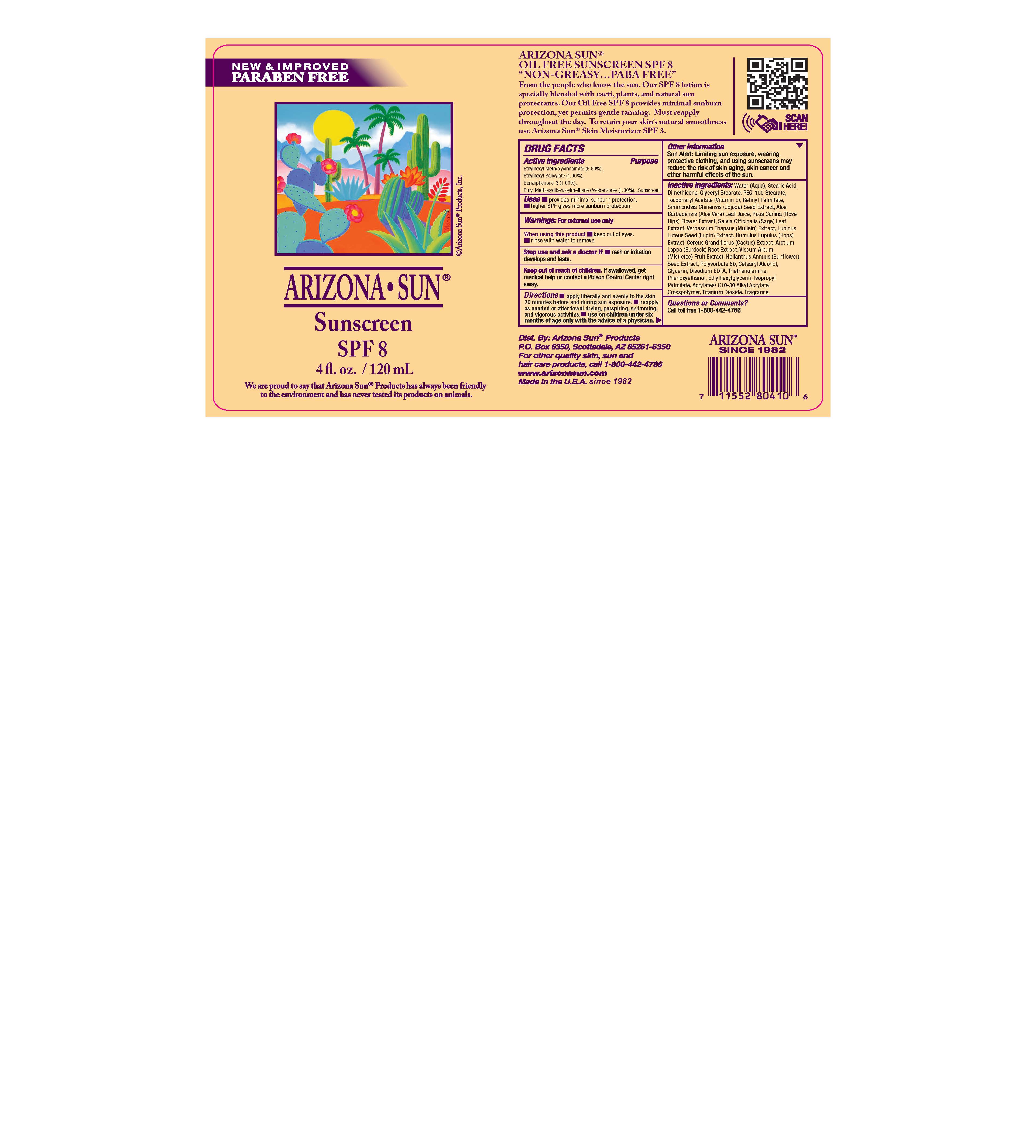 DRUG LABEL: Arizona Sun Sunscreen SPF 8
NDC: 61973-113 | Form: LOTION
Manufacturer: Arizona Sun Products
Category: otc | Type: HUMAN OTC DRUG LABEL
Date: 20240222

ACTIVE INGREDIENTS: OCTISALATE 10 mg/1 g; OXYBENZONE 10 mg/1 g; OCTINOXATE 65 mg/1 g; AVOBENZONE 10 mg/1 g
INACTIVE INGREDIENTS: ARCTIUM LAPPA ROOT; SUNFLOWER SEED; LUPINUS LUTEUS SEED; TITANIUM DIOXIDE; SAGE; MULLEIN LEAF; HOPS; STEARIC ACID; STEARYL ALCOHOL; ALOE VERA LEAF; DIMETHICONE; DISODIUM EDTA-COPPER; PEG-100 STEARATE; GLYCERIN; ACRYLATES/C10-30 ALKYL ACRYLATE CROSSPOLYMER (60000 MPA.S); VITAMIN A PALMITATE; SIMMONDSIA CHINENSIS SEED; POLYSORBATE 60; ROSA CANINA FLOWER; SELENICEREUS GRANDIFLORUS FLOWER; TROLAMINE; PHENOXYETHANOL; ETHYLHEXYLGLYCERIN; .ALPHA.-TOCOPHEROL ACETATE; WATER; VISCUM ALBUM FRUIT; ISOPROPYL PALMITATE; GLYCERYL STEARATE SE

Arizona Sun Sunscreen SPF 8

Active Ingredients

Ethylhexyl Methoxycinnamate (6.50%)

Ethylhexyl Salicylate (1.00%)

Benzophenone-3 (1.00%)

Butyl Methoxydibenzoylmethane (1.00%)

Purpose

Provides Minimal Sunburn Protection

Uses

Provides minimal sunburn protection. Higher SPF gives more sunburn protection.

Warnings

For external use only.

When using this product

keep out of eyes. Rinse with water to remove.

Stop and ask a doctor if

rash or irritation develops and lasts.

Keep out of the reach of children.

If swallowed get medical help or contact a poison control center right away.

Directions

Apply liberally and evenly to the skin 30 minutes before and during sun exposure. Reapply as needed or after towel drying, perspiring, swimming, and vigorous activities.

Other Information

Sun Alert: Limiting sun exposure, wearing protective clothing, and using suscreen may reduce the risk of skin aging, skin cancer and other harmful effects of the sun.

Inactive Ingredients

Water, Isopropyl Palmitate, Stearic Acid, Glyceryl Stearate, PEG-100 Stearate, Glycerin, Dimethicone, Cetearyl Alcohol, Tocopheryl Acetate (Vitamin E), Retinyl Palmitate, Simmondsia Chinensis (Jojoba) Seed Oil, Polysorbate 60, Aloe Barbadensis (Aloe Vera) Leaf Juice, Rosa Canina (Rose Hips) Flower Extract, Salvia Officinalis (Sage) Leaf Extract, Verbascum Thapsus (Mullein) Extract, Lupinus Luteus Seed (Lupin) Extract, Humulus Lupulus (Hops) Extract, Cereus Grandiflorus (Cactus) Extract, Arctium Lappa (Burdock) Root Extract, Viscum Album (Mistletoe) Fruit Extract, Helianthus Annuus (Sunflower) Seed Extract, Acrylates/ C10-30 Alkyl Acrylate Crosspolymer, Disodium EDTA, Triethanolamine, Phenoxyethanol, Ethylhexylglycerin, Fragrance , Titanium Dioxide

Questions?

Call toll free 1-800-442-4786